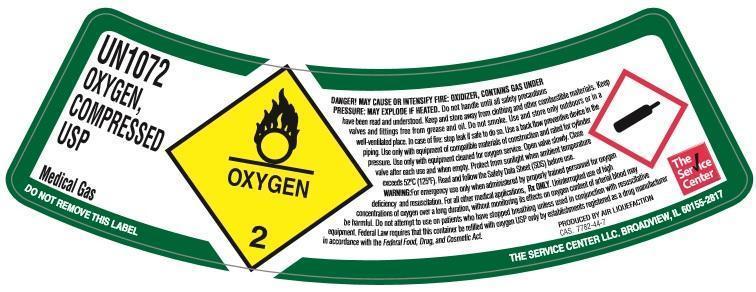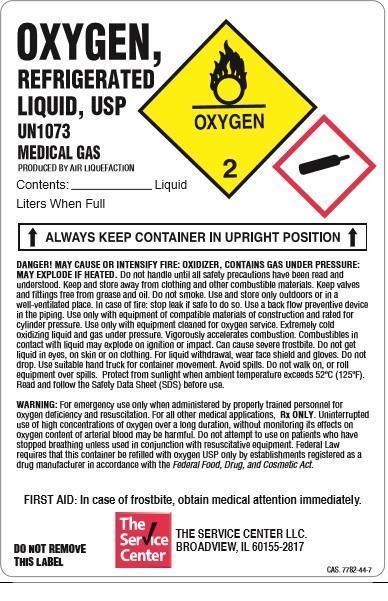 DRUG LABEL: Oxygen
NDC: 67024-001 | Form: GAS
Manufacturer: The Service Center LLC
Category: prescription | Type: HUMAN PRESCRIPTION DRUG LABEL
Date: 20151006

ACTIVE INGREDIENTS: Oxygen 992 mL/1 L

Oxygen

PACKAGE LABEL

US1072
OXYGEN, COMPRESSED USP
Medical Gas
DO NOT REMOVE THIS PRODUCT LABEL
OXYGEN 2
DANGER: MAY CAUSE OR INTENSIFY FIRE; OXIDIZER. CONTAINS GAS UNDER PRESSURE; MAY EXPLODE IF HEATED. Do not handle until all safety precautions have been read and understood. Keep and store away from clothing and other combustible materials. Keep valves and fittings free from grease and oil. Do not smoke. Use and store only outdoors or in a well-ventilated place. In case of fire: Stop leak if safe to do so. Use a back flow preventive device in the piping. Use only with equipment of compatible materials of construction and rated for cylinder pressure. Use only with equipment cleaned for oxygen service. Open valve slowly. Close valve after each use and when empty. Protect from sunlight when ambient temperature exceeds 52 degrees C (125 degrees F). Read and follow the Safety Data Sheet (SDS) before use.
WARNING: For emergency use only when administered by properly trained personnel for oxygen deficiency and resuscitation. For all other medical applications, Rx only. Uninterrupted use of high concentrations of oxygen over a long duration, without monitoring its effect on oxygen content of arterial blood, may be harmful. Do not attempt to use on patients who have stopped breathing unless used in conjunction with resuscitative equipment. Keep out of reach of children. Federal law requires that this container be refilled with oxygen USP only be establishments registered as a drug manufacturer in accordance with the Federal Food, Drug and Cosmetic Act.
CAS: 7782-44-7.
PRODUCED BY AIR LIQUEFACTION
THE SERVICE CENTER LLC
BROADVIEW, IL
60155-2817

PACKAGE LABEL

OXYGEN, REFRIGERATED LIQUID USP
UN1073
MEDICAL GAS
Produced by Air Liquefaction.
OXYGEN 2
CONTENTS: Liquid
Liters When Full
ALWAYS KEEP CONTAINER IN UPRIGHT POSITION
DANGER: MAY CAUSE OR INTENSIFY FIRE; OXIDIZER. CONTAINS GAS UNDER PRESSURE; MAY EXPLODE IF HEATED. Do not handle until all safety precautions have been read and understood. Keep and store away from clothing and other combustible materials. Keep valves and fittings free from grease and oil. Do not smoke. Use and store only outdoors or in a well-ventilated place. In case of fire: Stop leak if safe to do so. Use a back flow preventive device in the piping. Use only with equipment of compatible materials of construction and rated for cylinder pressure. Use only with equipment cleaned for oxygen service. Extremely cold oxidizing liquid may explode on ignition or impact. Can cause severe frostbite. Do not get liquid in eyes, on skin or on clothing. For liquid withdrawal, wear face shield and gloves. Do not drop. Use suitable hand truck for container movement. Avoid spills. Do not walk on, or roll equipment over spills. Protect from sunlight when ambient temperature exceeds 52 degrees C (125 degrees F). Read and follow the Safety Data Sheet (SDS) before use.

WARNING: USP For emergency use only when administered by properly trained personnel for oxygen deficiency and resuscitation. For all other medical applications, Rx only. Uninterrupted use of high concentrations of oxygen over a long duration, without monitoring its effect on oxygen content of arterial blood, may be harmful. Do not attempt to use on patients who have stopped breathing unless used in conjunction with resuscitative equipment. Keep out of reach of children. Federal law requires that this container be refilled with oxygen USP only be establishments registered as a drug manufacturer in accordance with the Federal Food, Drug and Cosmetic Act.
FIRST AID: In case of frostbite, obtain medical attention immediately.
DO NOT REMOVE THIS PRODUCT LABEL.
THE SERVICE CENTER LLC
BROADVIEW, IL 60155-2817